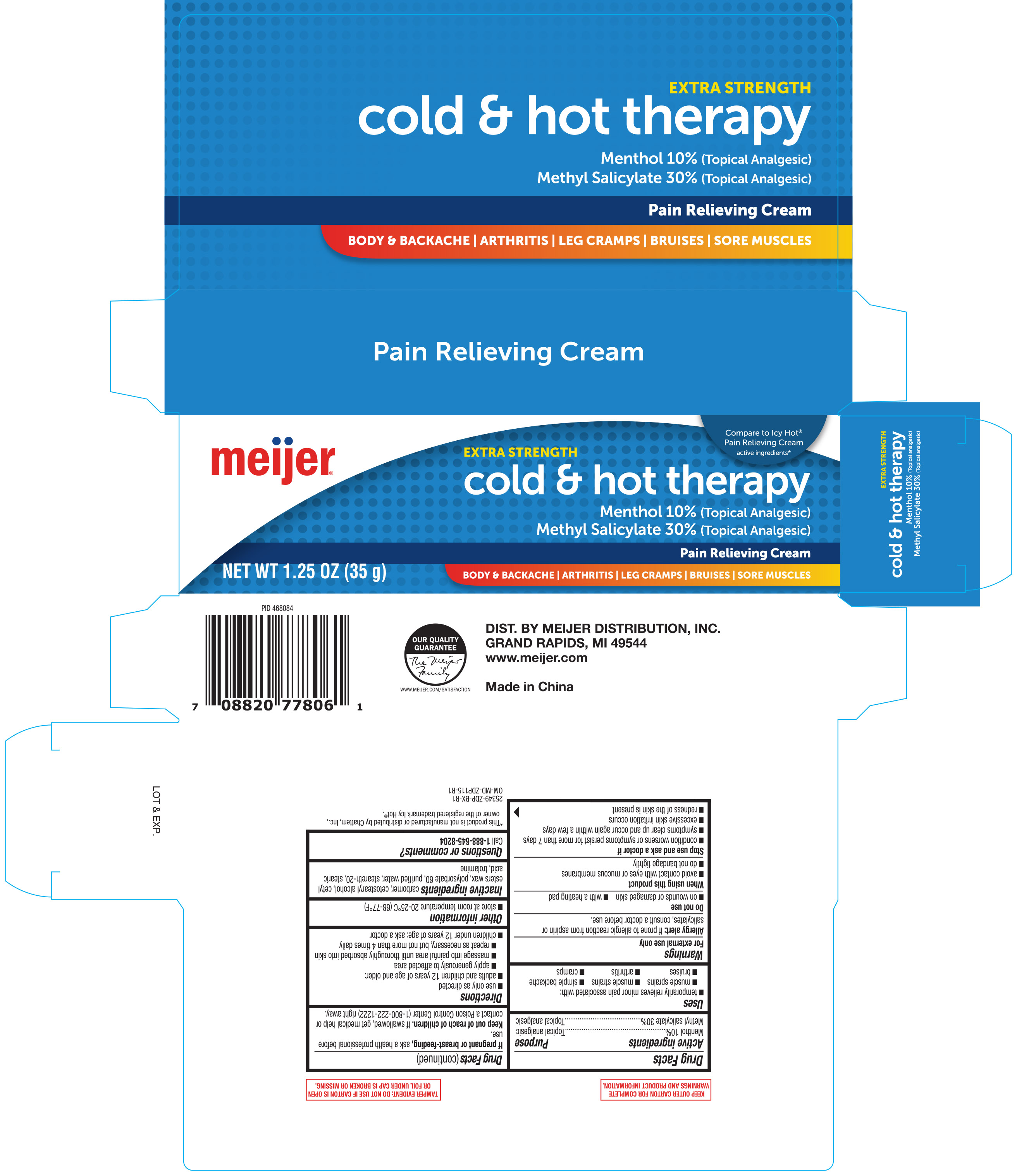 DRUG LABEL: Meijer Cold and Hot Therapy
NDC: 41250-858 | Form: CREAM
Manufacturer: Meijer, Inc.
Category: otc | Type: HUMAN OTC DRUG LABEL
Date: 20221215

ACTIVE INGREDIENTS: MENTHOL 10 g/100 g; METHYL SALICYLATE 30 g/100 g
INACTIVE INGREDIENTS: TROLAMINE; STEARIC ACID; CARBOMER HOMOPOLYMER, UNSPECIFIED TYPE; CETOSTEARYL ALCOHOL; WATER; STEARETH-20; POLYSORBATE 60; CETYL ESTERS WAX

Meijer Cold & Hot Therapy Pain Relieving Cream 1.25oz 25349 ZDP

Active Ingredients Purpose

Menthol 10%.................................................Topical Analgesic

Methyl Salicylate 30%...................................Topical Analgesic

Uses

temporarily relieves minor pain associated with:

- muscle sprains
- muscle strains
- simple backache
- bruises
- arthritis
- cramps

Warnings

For external use only

Allergy alert: If prone to allergic reaction from aspirin or salicylates, consult a doctor before use.

Do not use

- on wounds or damaged skin
- with a heating pad

When using this product

- avoid contact with eyes or mucous membranes
- do not bandage tightly

Stop use and ask a doctor if

- condition worsens or symptoms persist for more than 7 days
- symptoms clear up and occur again within a few days
- excessive skin irritation occurs
- redness of the skin is present

PREGNANCY OR BREAST FEEDING

If pregnant or breast-feeding, ask a health professional before use.

Keep out of reach of children. If swallowed, get medical help or contact a Poison Control Center (1-800-222-1222) right away.

Directions

use only as directed

adults and children 12 years of age and older:

- apply generously to affected area
- massage into painful area until thoroughly absorbed into skin
- repeat as necessary, but not more than 4 times daily

childen under 12 years of age: ask a doctor

Other Information

- store at room temperature 20-25ºC (68-77ºF)

INACTIVE INGREDIENT

Inactive ingredients carbomer, cetostearyl alcohol, cetyl esters wax, polysorbate 60, purified water, steareth-20, stearic acid, trolamine